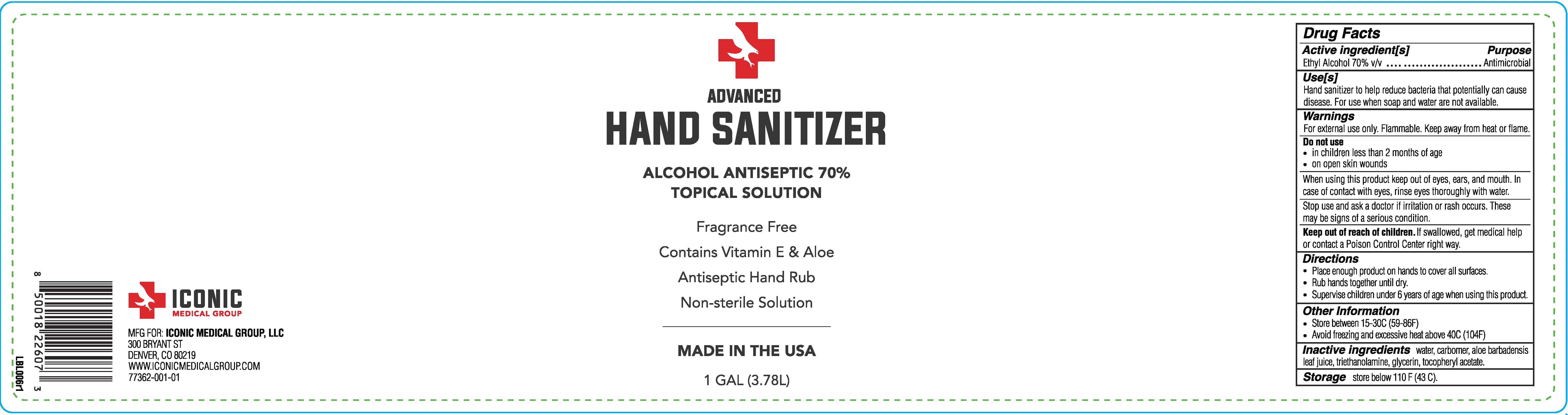 DRUG LABEL: Iconic 70% Hand Sanitizer Gel
NDC: 77362-001 | Form: GEL
Manufacturer: Iconic Medical Group, LLC
Category: otc | Type: HUMAN OTC DRUG LABEL
Date: 20200701

ACTIVE INGREDIENTS: ALCOHOL 2.649787 L/3.78541 L
INACTIVE INGREDIENTS: WATER; .ALPHA.-TOCOPHEROL ACETATE; ALOE VERA LEAF; CARBOMER HOMOPOLYMER, UNSPECIFIED TYPE; TROLAMINE; GLYCERIN

Iconic 70% Hand Sanitizer 1 Gallon

Container label

1 gallon NDC: 77362-001-01